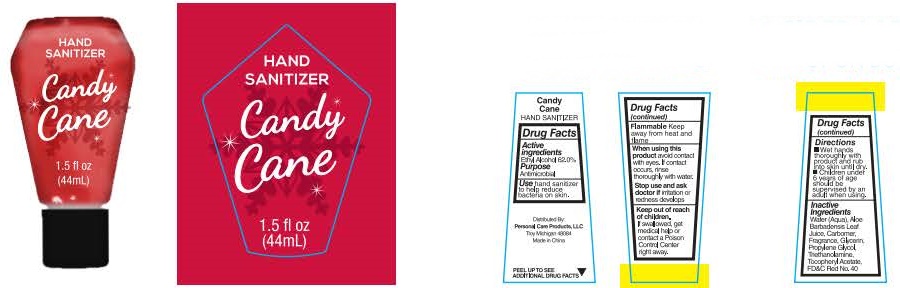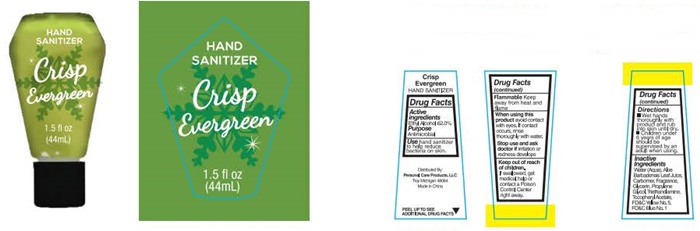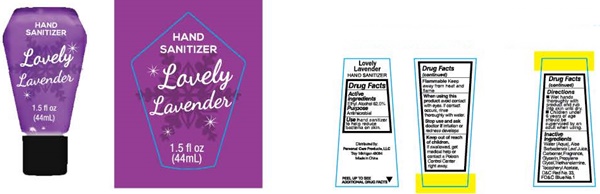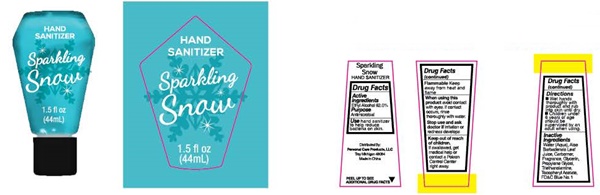 DRUG LABEL: Candy Cane
NDC: 29500-9393 | Form: LIQUID
Manufacturer: Personal Care Products LLC
Category: otc | Type: HUMAN OTC DRUG LABEL
Date: 20160906

ACTIVE INGREDIENTS: ALCOHOL 26.36 g/44 mL
INACTIVE INGREDIENTS: WATER; ALOE VERA LEAF; CARBOXYPOLYMETHYLENE; GLYCERIN; PROPYLENE GLYCOL; TROLAMINE; .ALPHA.-TOCOPHEROL ACETATE; FD&C RED NO. 40

Lovely Lavender - 9396
Sparkling Snow - 9395
Crisp Evergreen - 9394
Candy Cane - 9393

Drug Facts Active ingredients

Ethyl Alcohol 62.0%

Purpose

Antimicrobial

Keep out of reach of children.

If swallowed get medical help or contact a Poison Control Center right away.

Use

hand sanitizer to help reduce bacteria on skin.

Flammable

Keep away from heat and flame.

When using thie product

avoid contact with eyes. If contact occurs, rinse thoroughly with water.

Stop use and ask a doctoroif

irritation or redness develops.

Directions

- Wet hands thoroughly with product and rub into skin until dry.
- Children under 6 years of age should be supervised by an adult when using.

Inactive ingredients

Water (Aqua), Aloe Barbadensis Leaf Juice, Carbomer, Fragrance, Glycerin, Propylene Glycol, Triethanolamine, Tocopheryl Acetate. FD&C Blue No. 1, FD&C Red No. 40, FD&C Yellow No. 5, D&C Red No. 33

Lovely Lavender Sparkling Snow Crisp Evergreen Candy Cane

Hand Sanitizer
Lovely Lavender

1.5 fl oz
(44mL)

Distributed By:
Personal Care Products, LLC
Troy, Michigan 49064
Made in China

PEEL UP TO SEE
ADDITIONAL DRUG FACTS

Hand Sanitizer
Sparkling Snow

1.5 fl oz
(44mL)

Distributed By:
Personal Care Products, LLC
Troy, Michigan 49064
Made in China

PEEL UP TO SEE
ADDITIONAL DRUG FACTS

Hand Sanitizer
Crisp Evergreen

1.5 fl oz
(44mL)

Distributed By:
Personal Care Products, LLC
Troy, Michigan 49064
Made in China

PEEL UP TO SEE
ADDITIONAL DRUG FACTS

Hand Sanitizer
Candy Cane

1.5 fl oz
(44mL)

Distributed By:
Personal Care Products, LLC
Troy, Michigan 49064
Made in China

PEEL UP TO SEE
ADDITIONAL DRUG FACTS